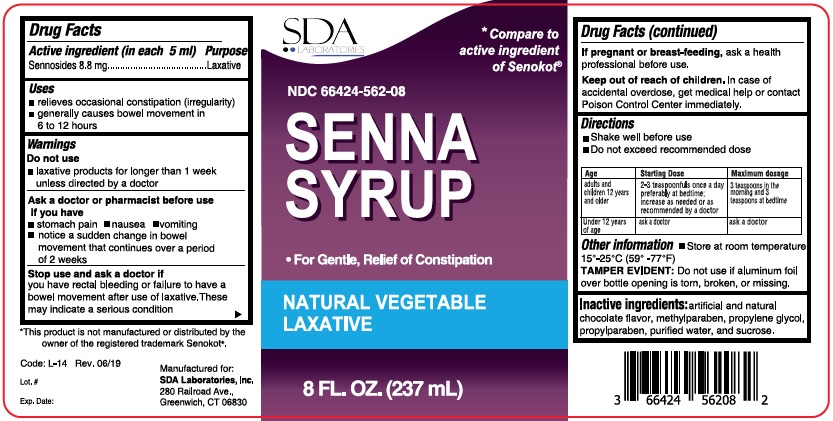 DRUG LABEL: SENNA Syrup
NDC: 66424-562 | Form: SYRUP
Manufacturer: SDA Laboratories, Inc.
Category: otc | Type: HUMAN OTC DRUG LABEL
Date: 20241220

ACTIVE INGREDIENTS: SENNOSIDES A AND B 8.8 mg/5 mL
INACTIVE INGREDIENTS: METHYLPARABEN; PROPYLPARABEN; SUCROSE; WATER

SDA- Senna 562

Active ingredient (in each 5 ml)

Sennosides 8.8 mg

Purpose

Laxative

Uses

• relieves occasional constipation (irregularity)
• generally causes bowel movement in 6 to 12 hours

Warnings

Do not use

• laxative products for longer than 1 week unless directed by a doctor

Ask a doctor or pharmacist before use if you have

• stomach pain • nausea • vomiting

• notice a sudden change in bowel movement that continues over a period of 2 weeks

Stop use and ask a doctor if

you have rectal bleeding or failure to have a bowel movement after use of laxative. These may indicate a serious condition

If pregnant or breast-feeding,ask a health professional before use

Keep out of reach of children.In case of accidental overdose, get medical help or contact a Poison Control Center immediately.

Directions

• shake well before use
• take preferably at bedtime or as directed by a doctor

Age | Starting Dose | Maximum dosage
adults and children; 12 years and older | 2-3 teaspoonfuls once a day | 3 teaspoonfuls twice a day
6 years to under; 12 years of age | 1-1½ teaspoonfuls once a day | 1½ teaspoonfuls twice; a day
2 to under 6 years; of age | 1/2-3/4 teaspoon once a day | 3/4 teaspoon twice a day
under 2 years of age | ask a doctor | ask a doctor

Other information

• Store at room temperature 15°-30°C (59°-86°F)

TAMPER EVIDENT:Do not use this product if breakaway band on cap is broken or missing

Inactive ingredient:

flavors, methyl paraben, propyl paraben, sucrose and water.

QUESTIONS

TO REPORT ADVERSE DRUG EVENTS CALL 800-687-0176

Natural Vegetable Laxative

For Gentle, Relief of Constipation

* Compare to Active ingredient of Senokot®

* This product is not manufactured or distributed by the owner of the registered trademark Senokot®

Distributed By: SDA Laboratories Inc.

280 Railroad Ave. Greenwich, CT. 06830